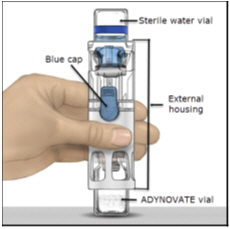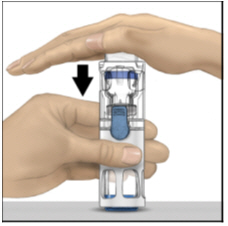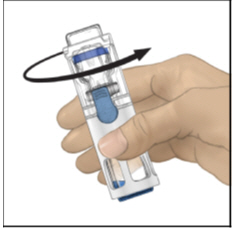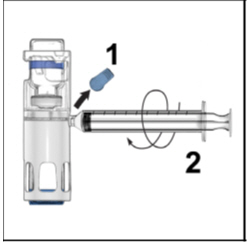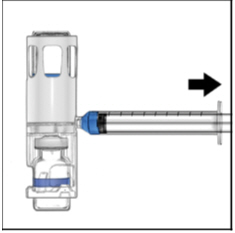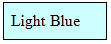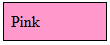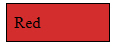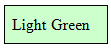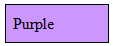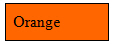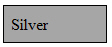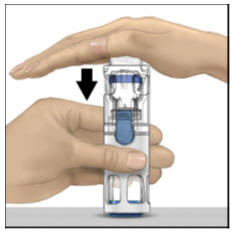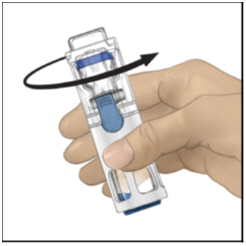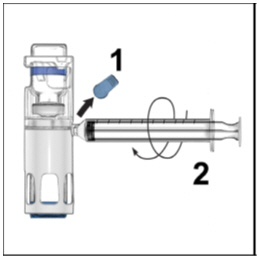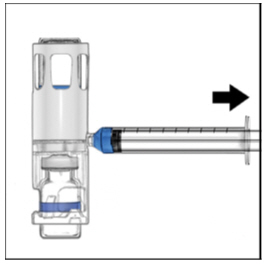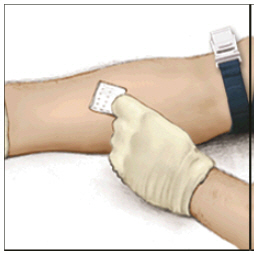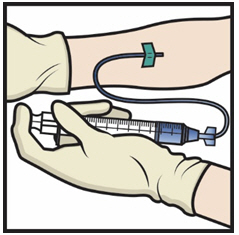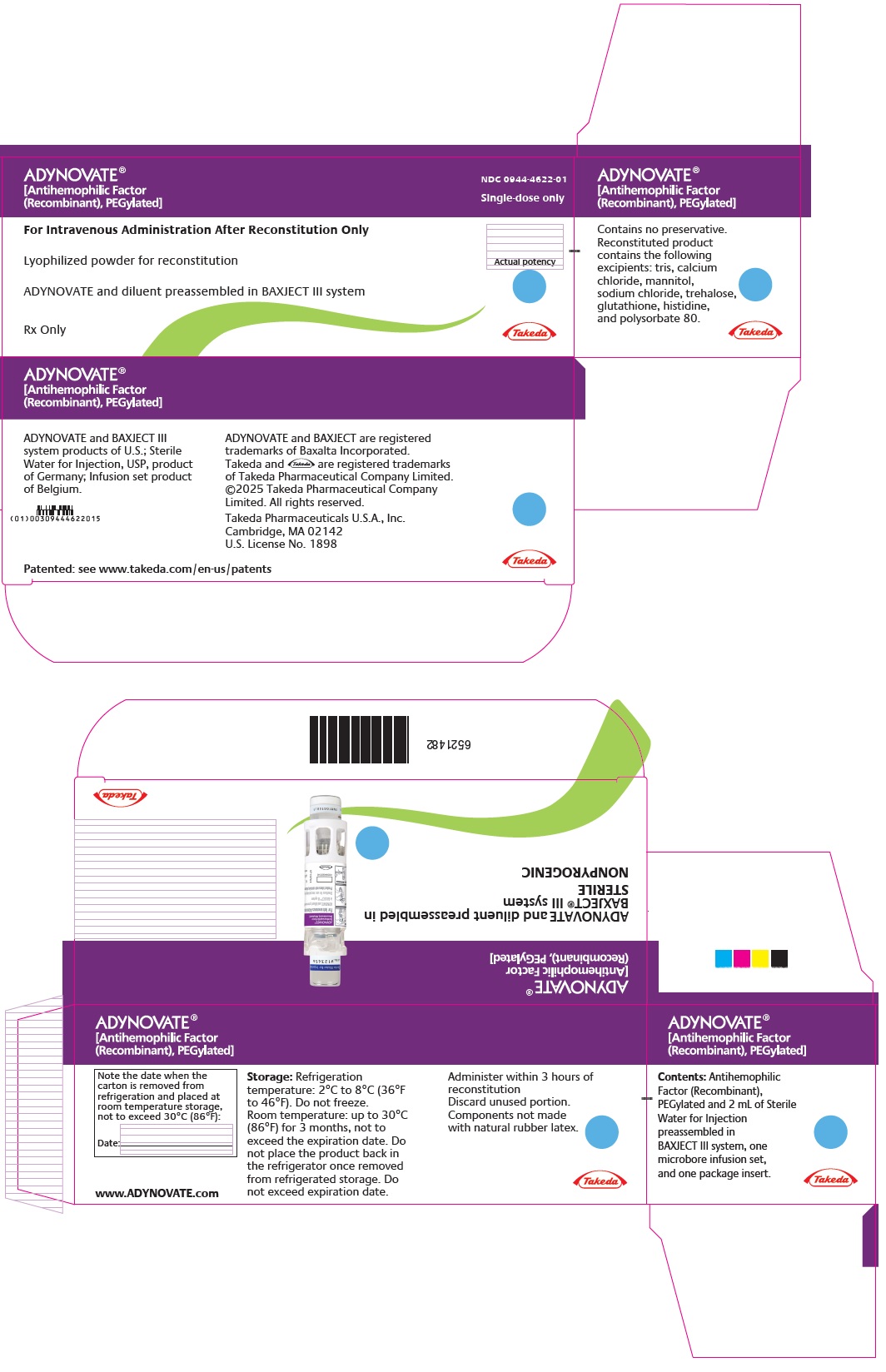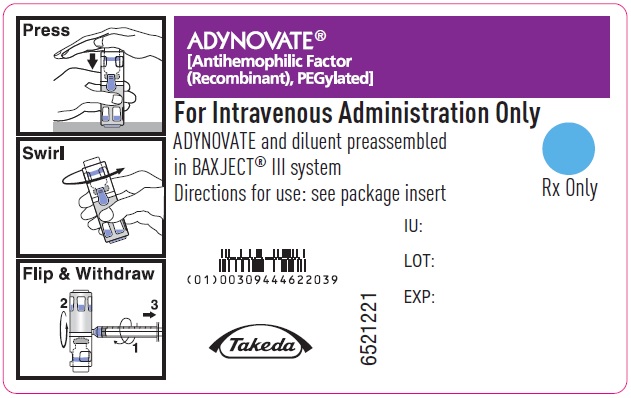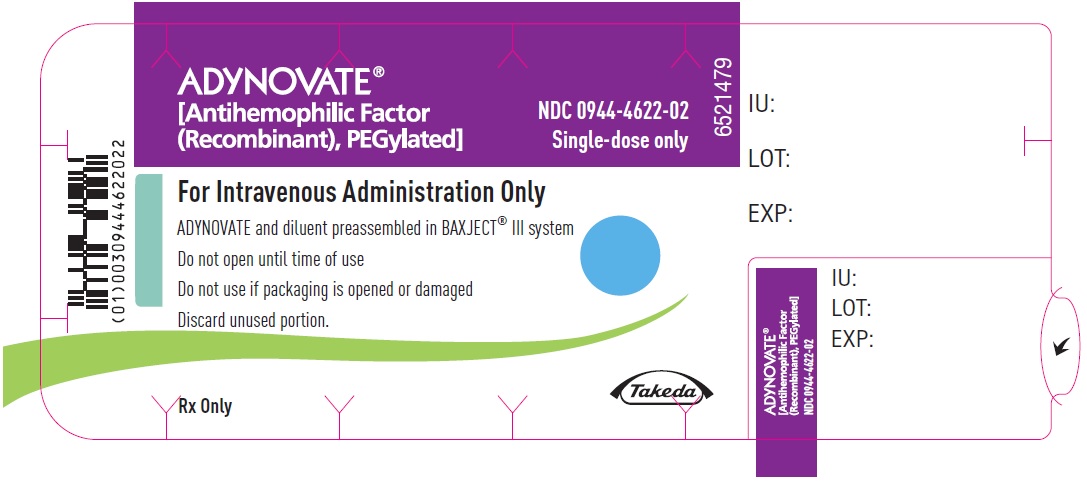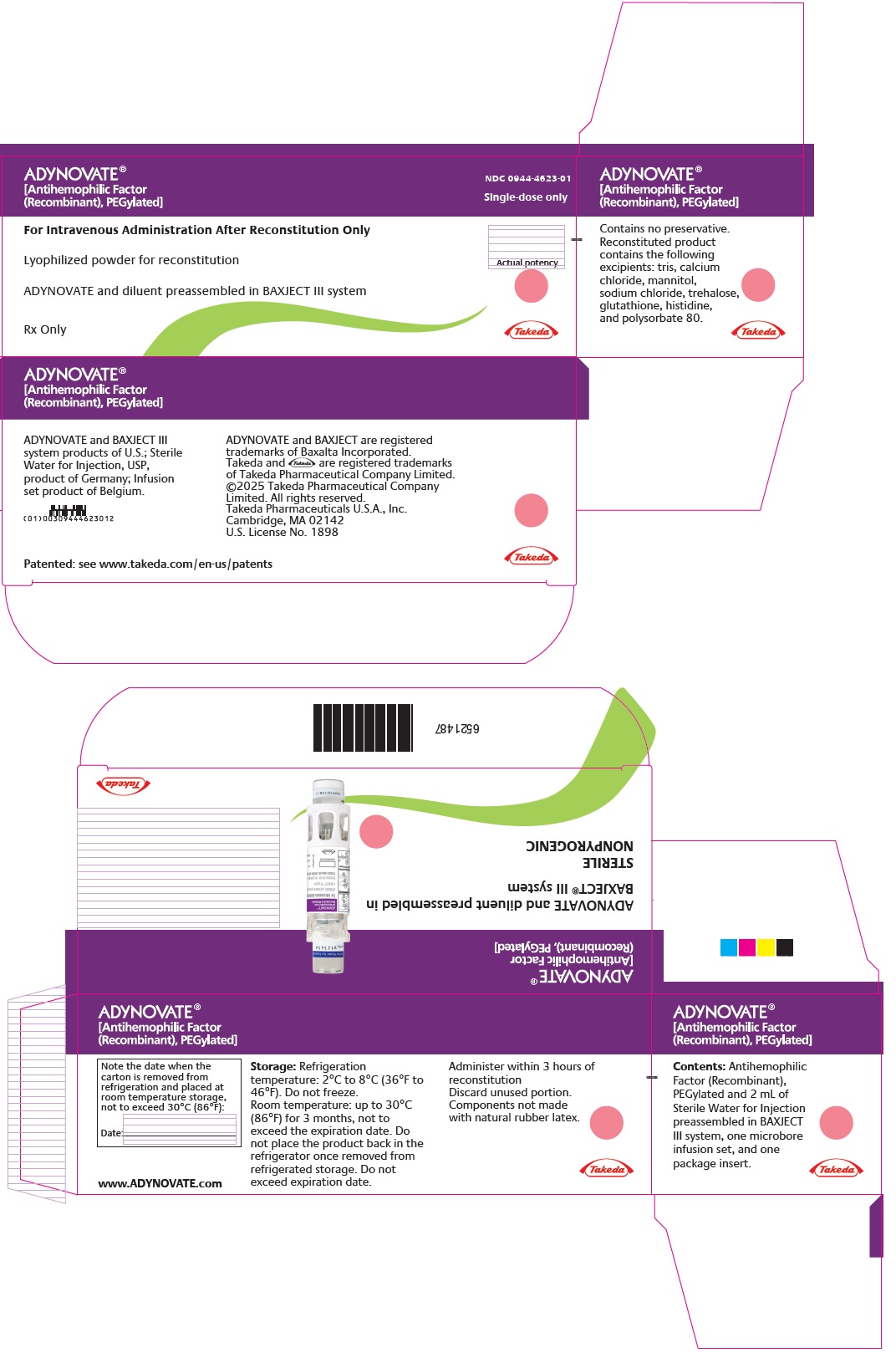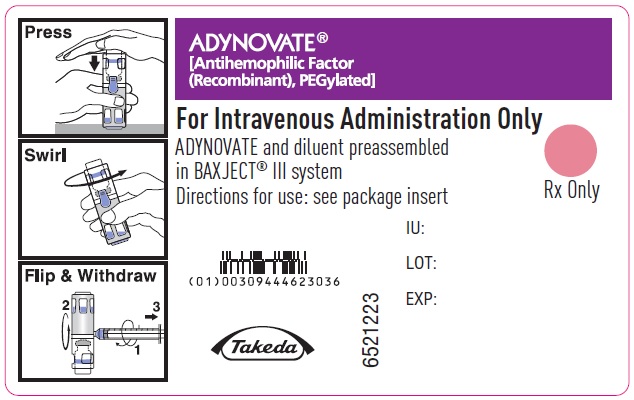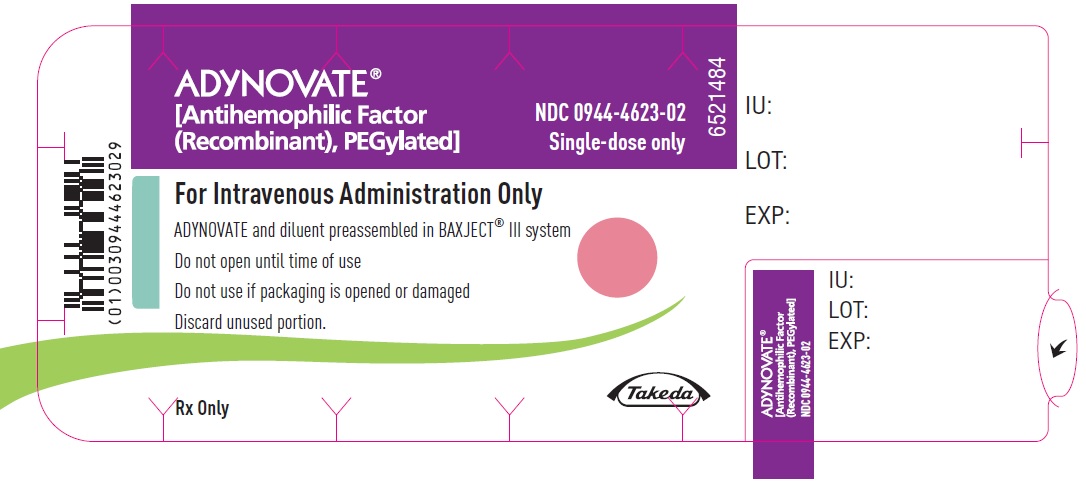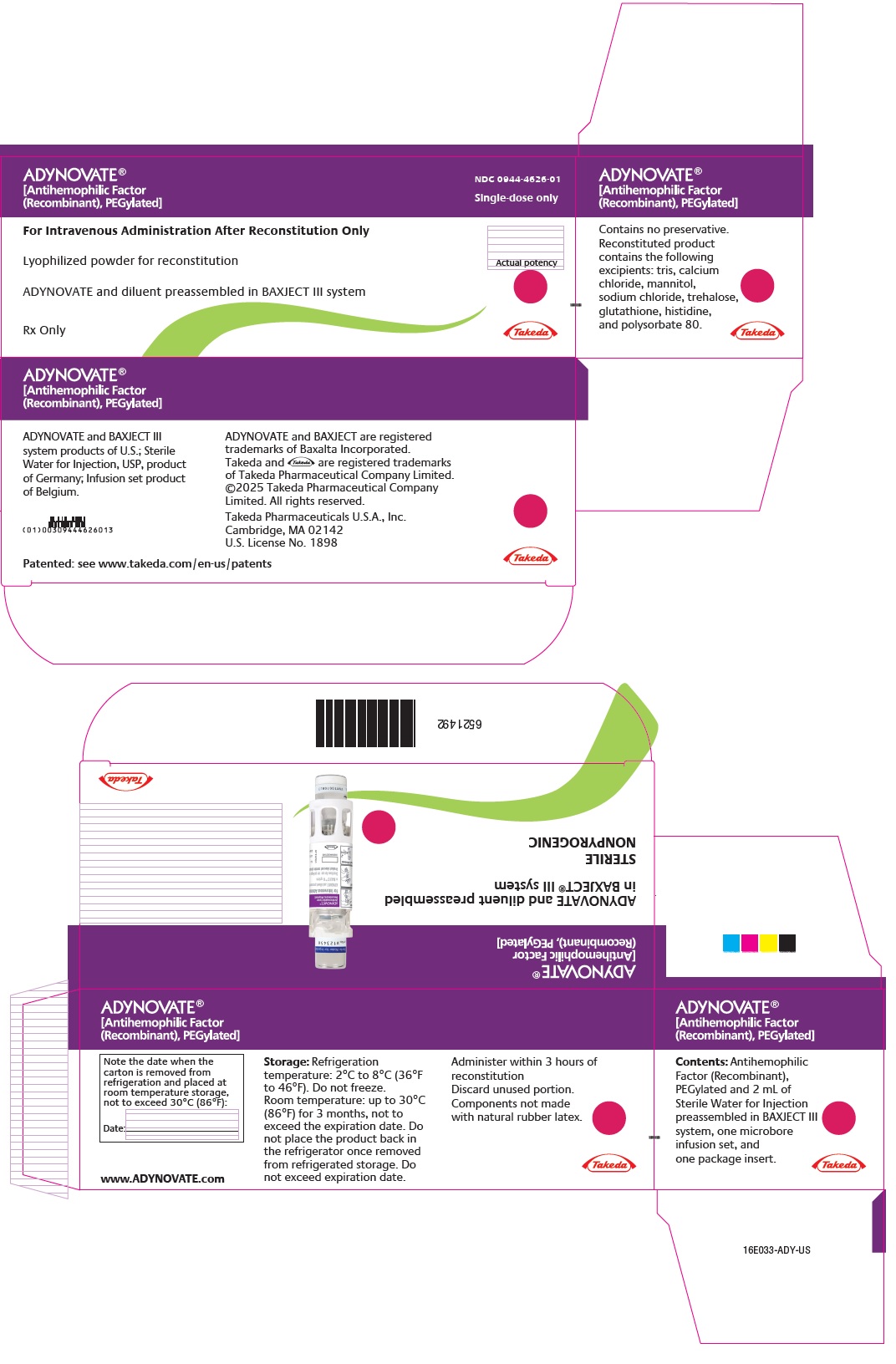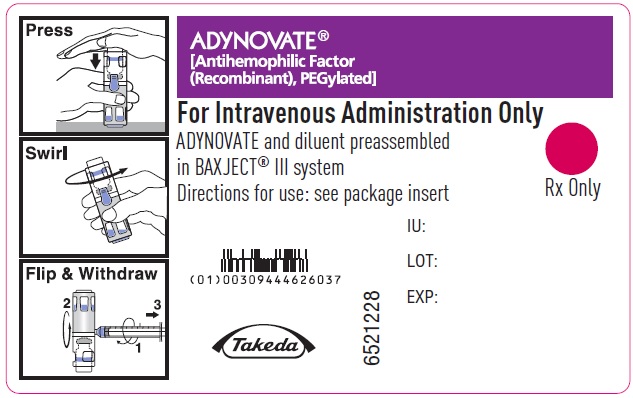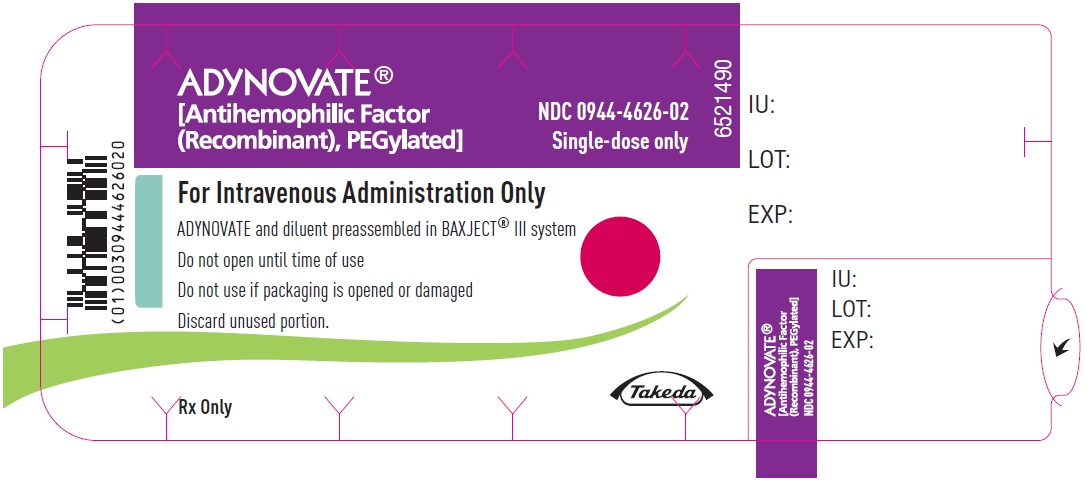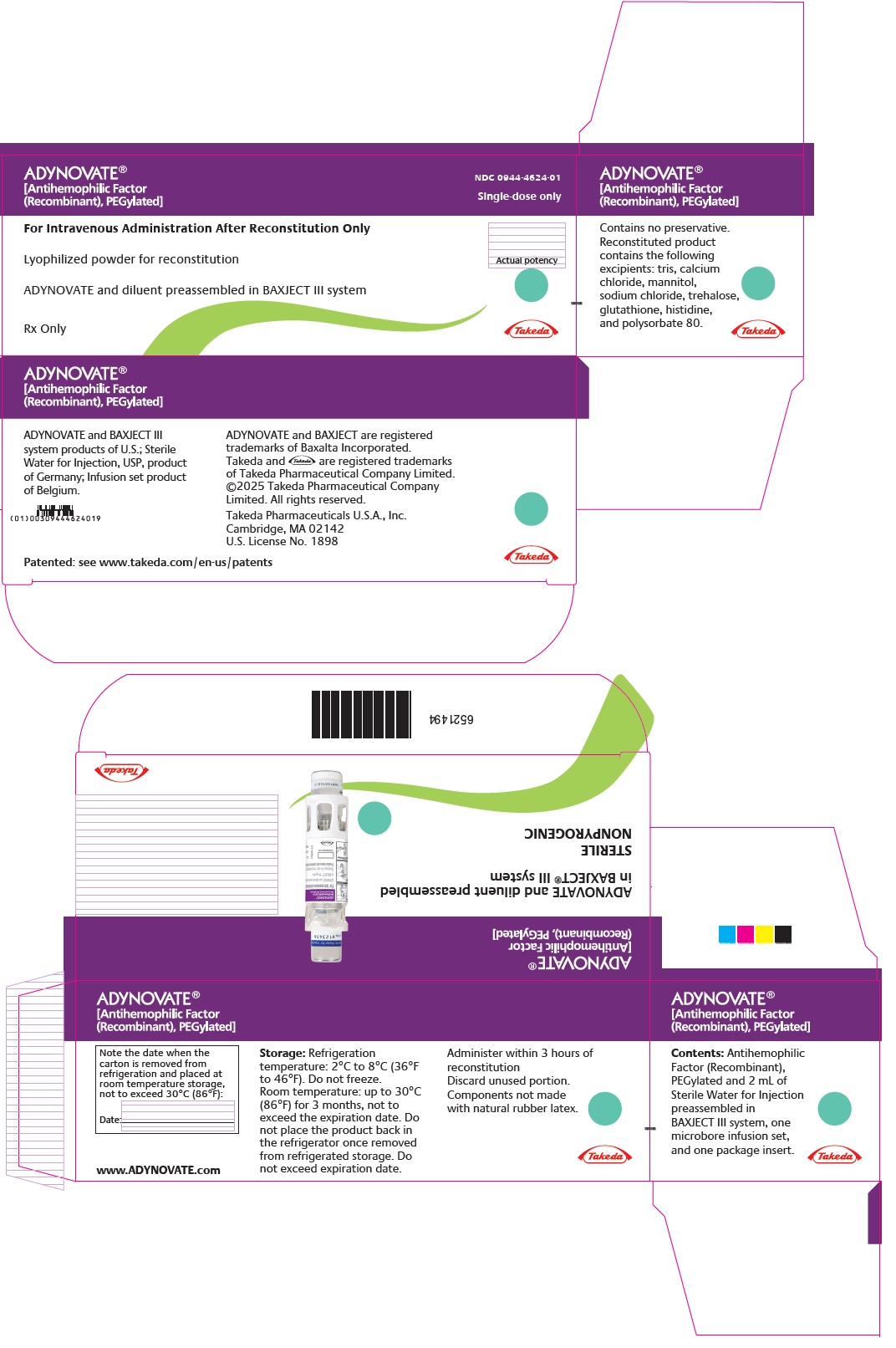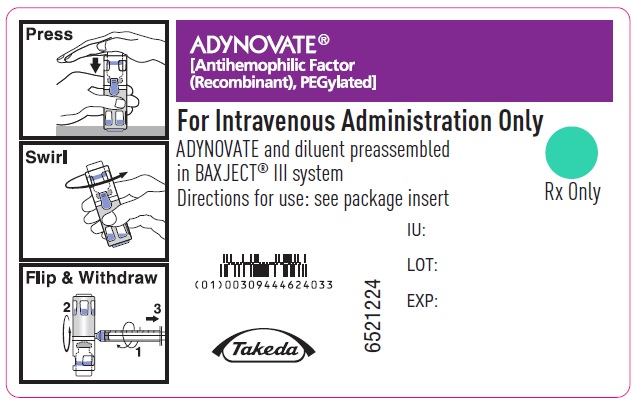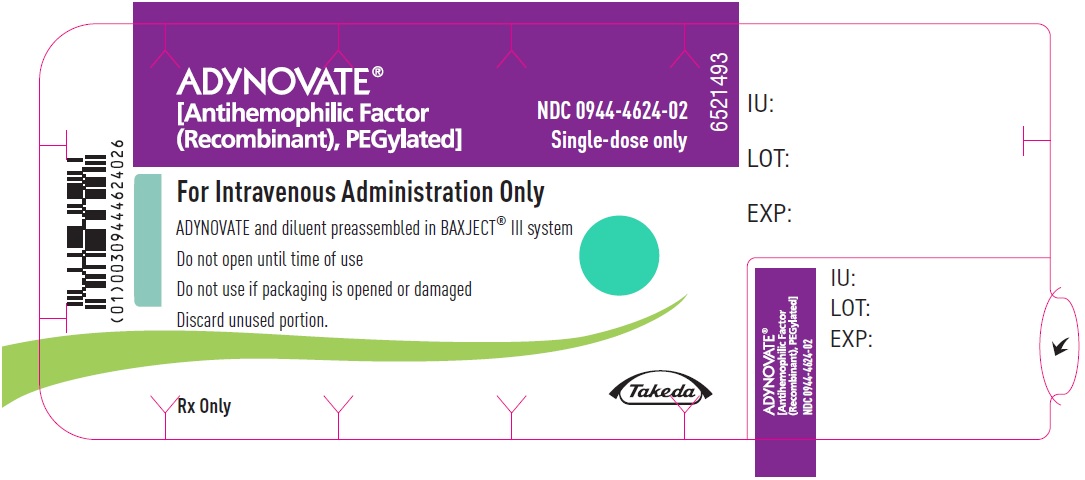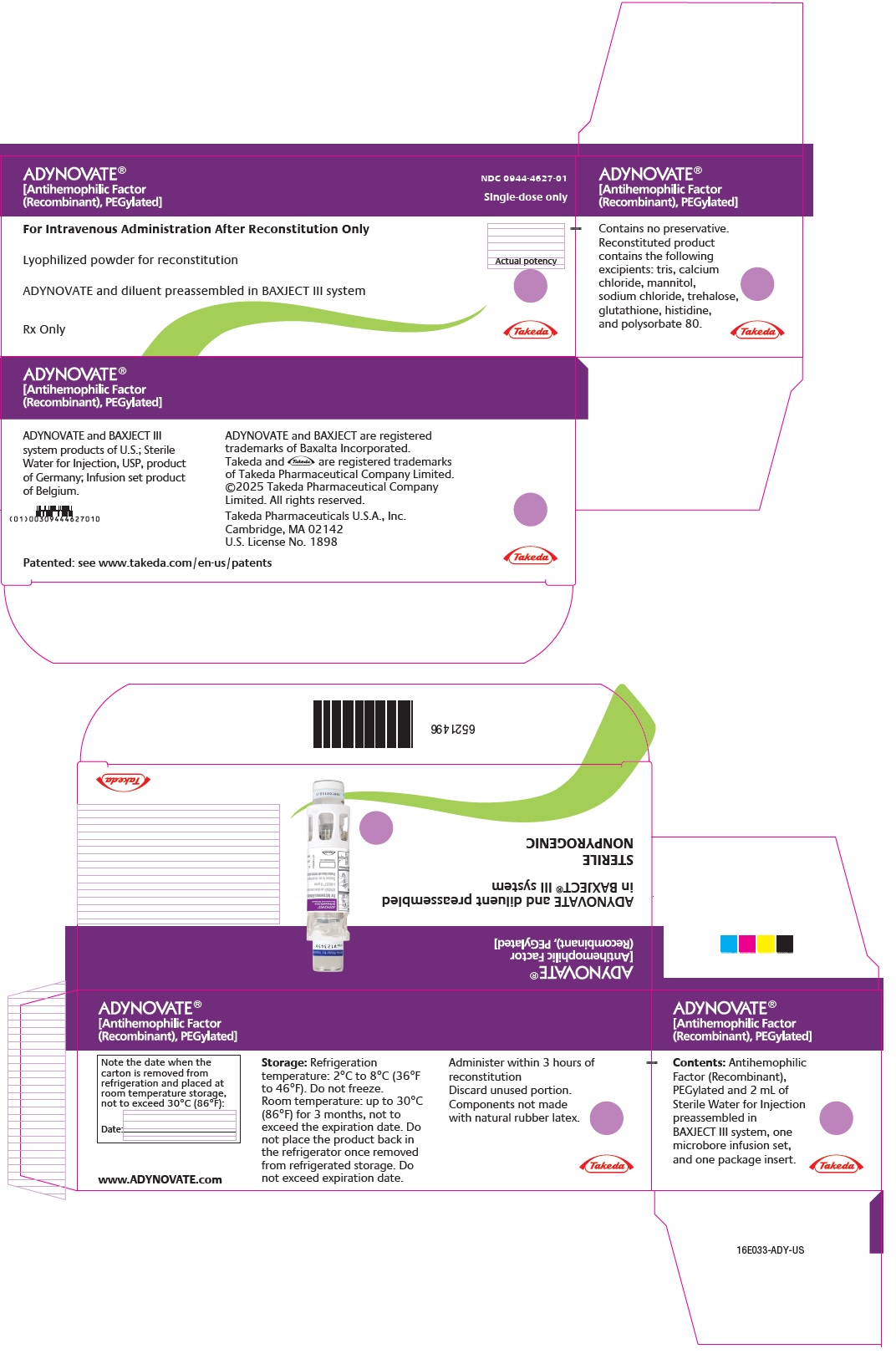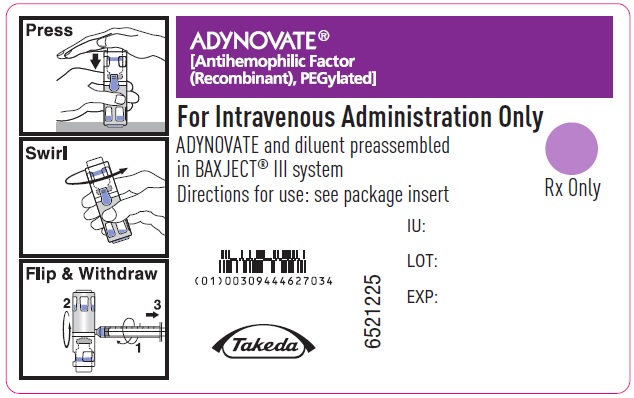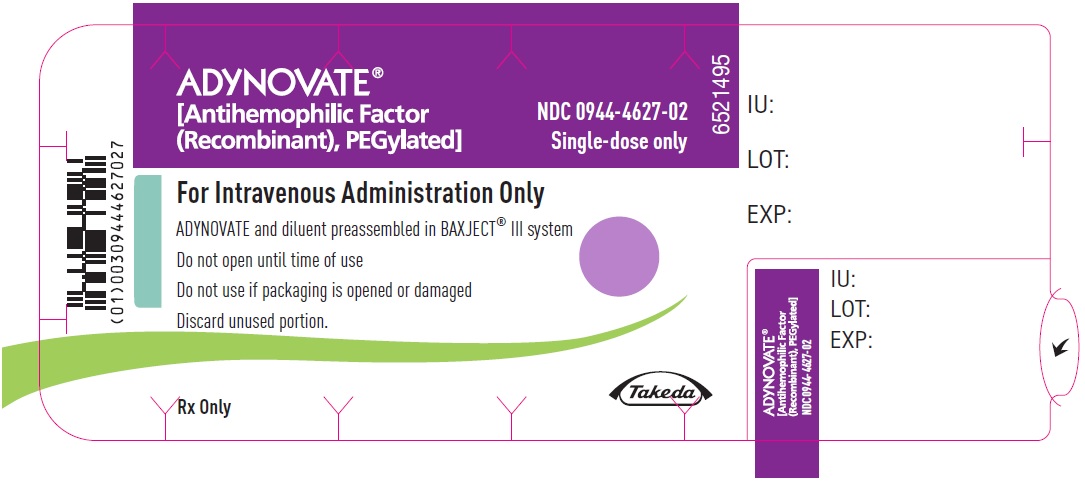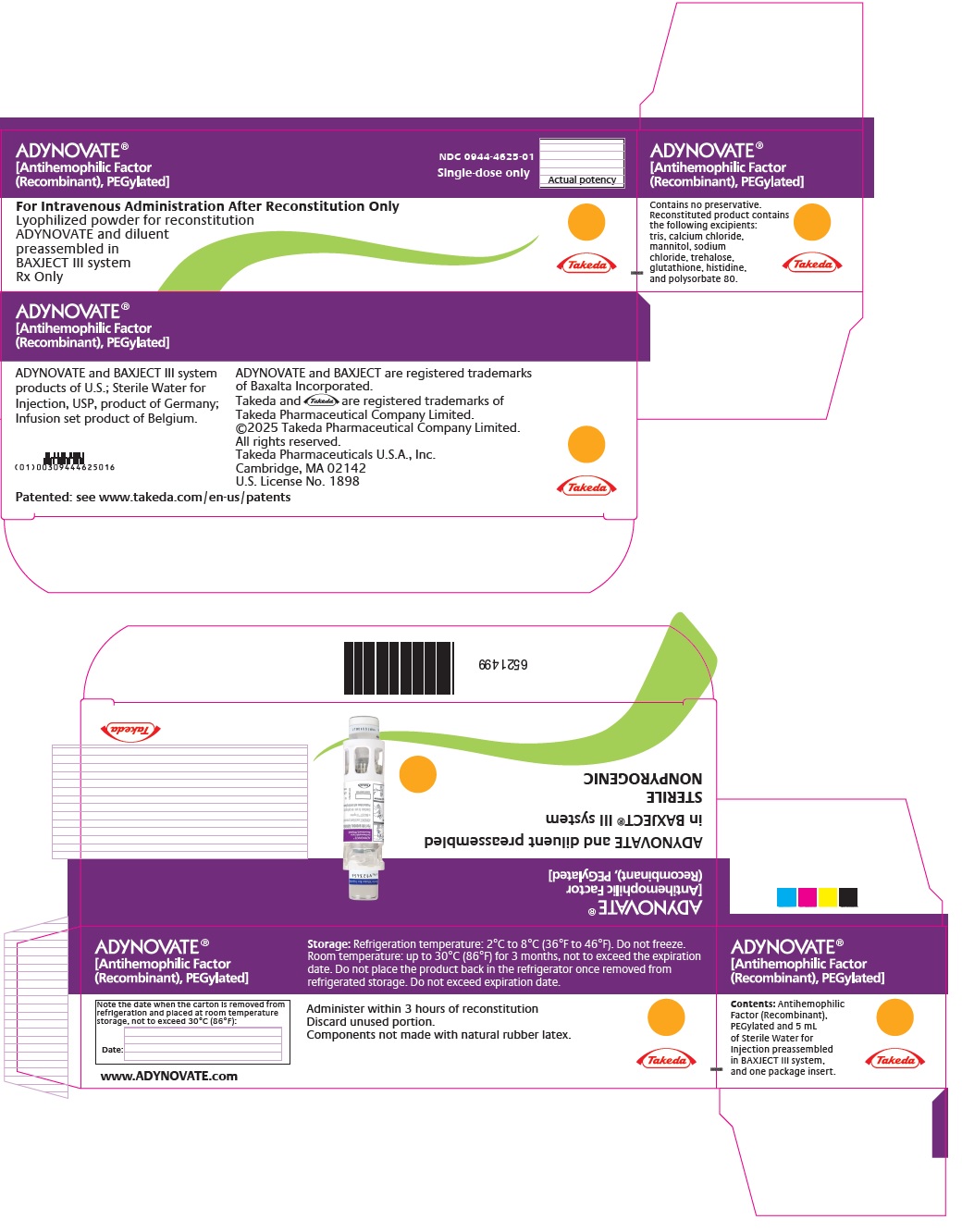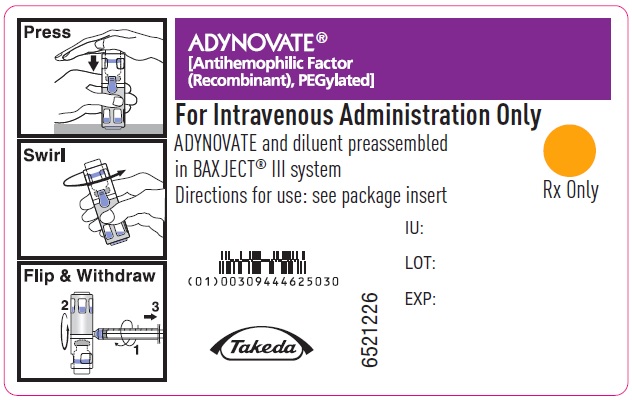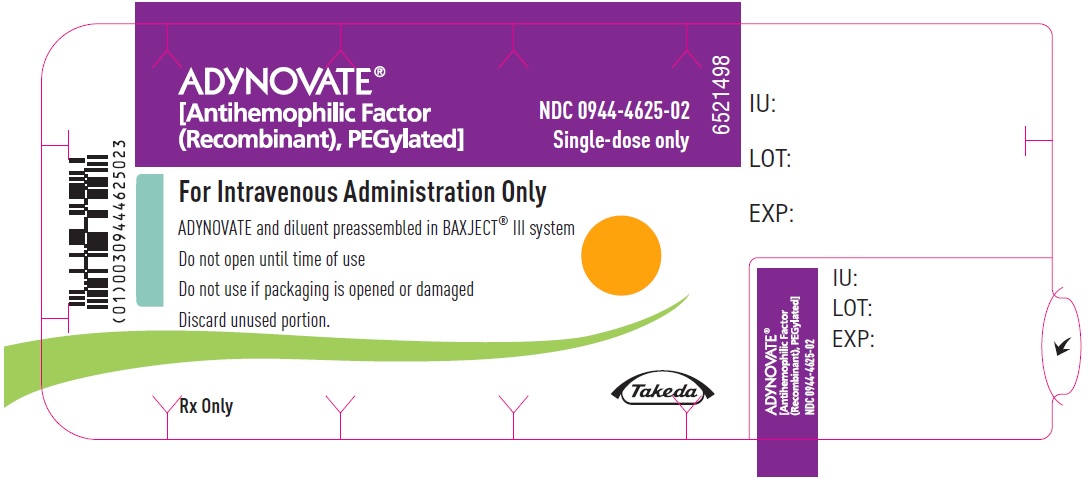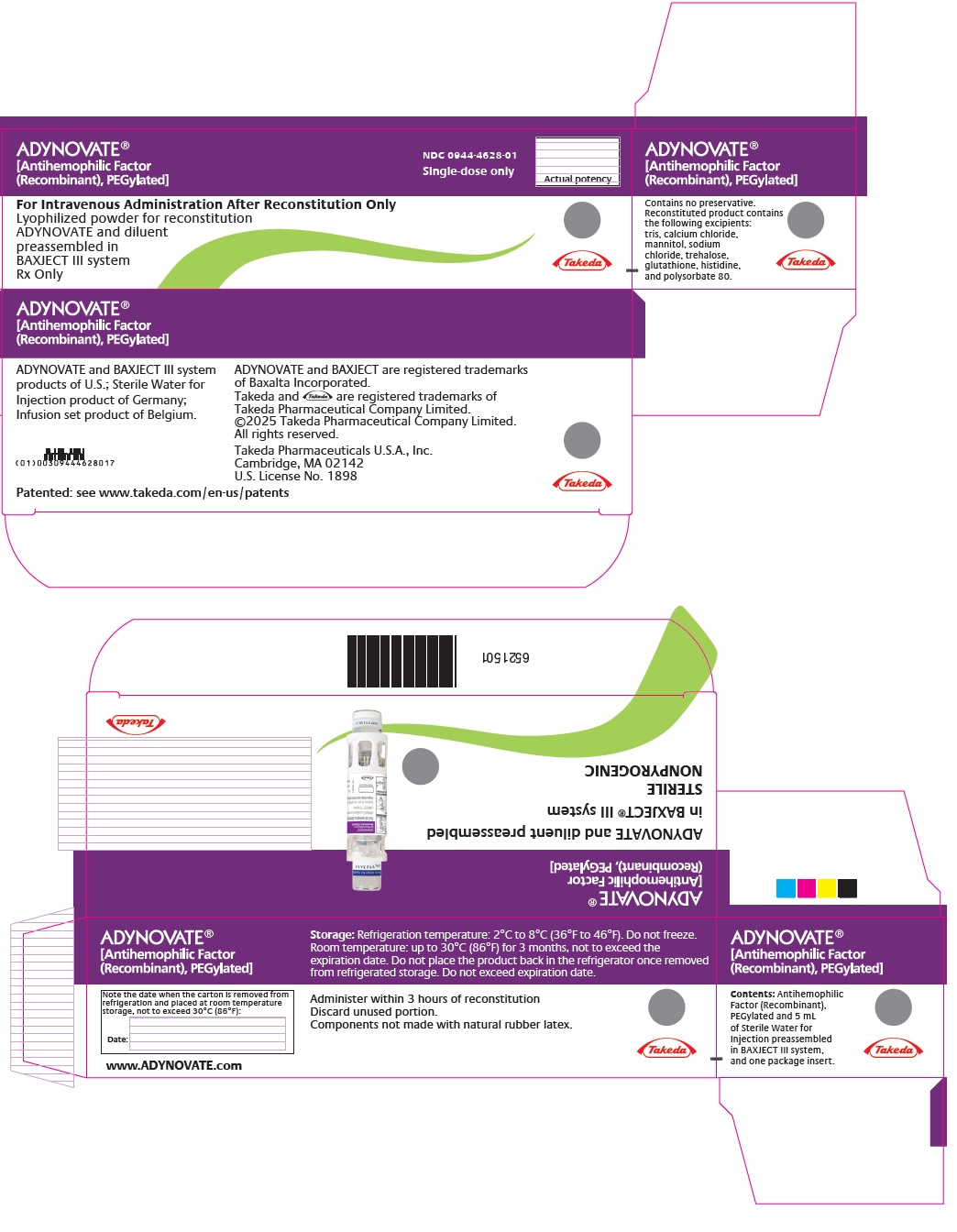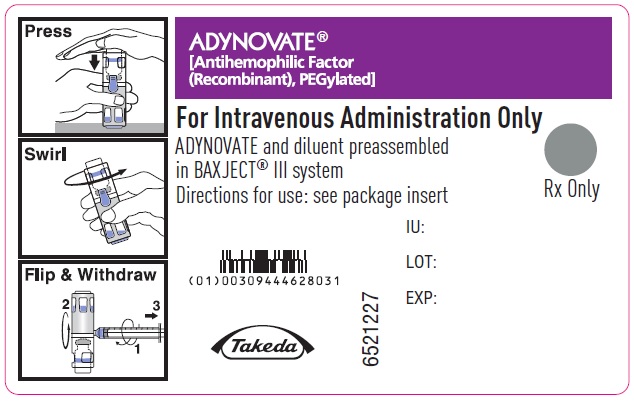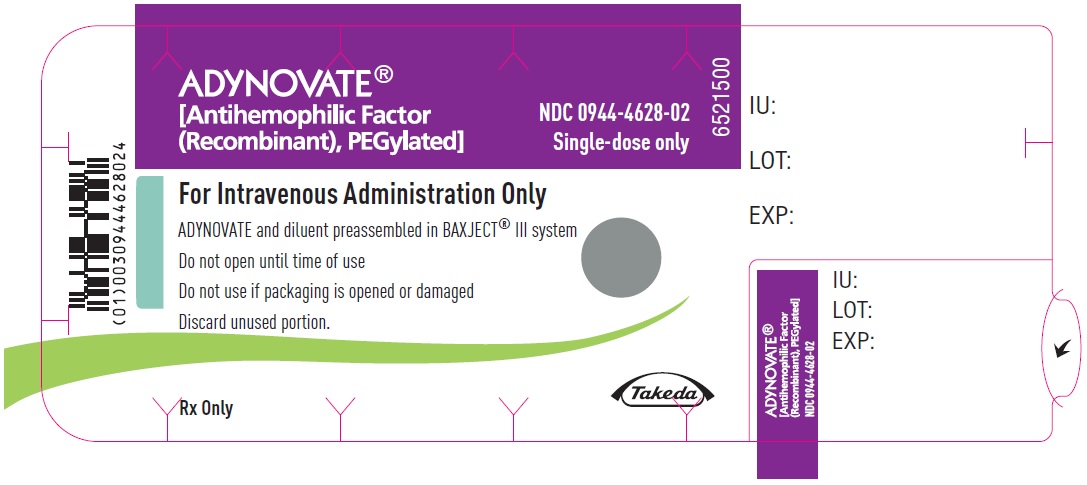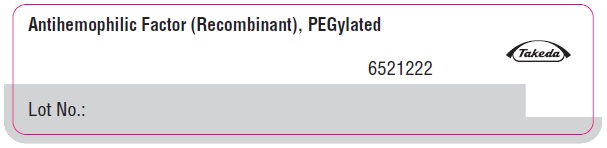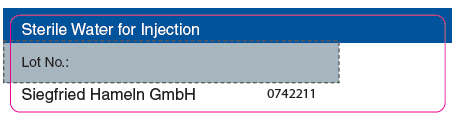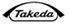 DRUG LABEL: ADYNOVATE
NDC: 0944-4622 | Form: KIT | Route: INTRAVENOUS
Manufacturer: Takeda Pharmaceuticals Amercia, Inc.
Category: other | Type: PLASMA DERIVATIVE
Date: 20251016

ACTIVE INGREDIENTS: ANTIHEMOPHILIC FACTOR, HUMAN RECOMBINANT 250 [iU]/2 mL
INACTIVE INGREDIENTS: TROMETHAMINE; CALCIUM CHLORIDE; MANNITOL; SODIUM CHLORIDE; TREHALOSE DIHYDRATE; GLUTATHIONE; HISTIDINE; POLYSORBATE 80; WATER 1 mL/1 mL

HIGHLIGHTS OF PRESCRIBING INFORMATION

These highlights do not include all the information needed to use ADYNOVATE® safely and effectively. See full prescribing information for ADYNOVATE.
ADYNOVATE, (Antihemophilic Factor, Recombinant, PEGylated) Lyophilized Powder for Solution for Intravenous Injection
Initial U.S. Approval: 2015

1 INDICATIONS AND USAGE

ADYNOVATE, Antihemophilic Factor (Recombinant), PEGylated, is a human antihemophilic factor indicated in adult and pediatric patients with hemophilia A (congenital factor VIII deficiency) for:

- On-demand treatment and control of bleeding episodes. (1)
- Perioperative management. (1)
- Routine prophylaxis to reduce the frequency of bleeding episodes. (1)

Limitations of Use

ADYNOVATE is not indicated for the treatment of von Willebrand disease. (1)

2 DOSAGE AND ADMINISTRATION

For intravenous use after reconstitution only.

- One unit per kilogram body weight will raise the factor VIII level by 2% international units per deciliter (IU per dL). Each vial of ADYNOVATE is labeled with the actual amount of recombinant factor VIII present in IU. (2.1)
- On-demand treatment and control of bleeding episodes and perioperative management:
  - Estimated Increment of factor VIII (IU/dL or % of normal) = [Total Dose (IU)/body weight (kg)] × 2 (IU/dL per IU/kg) (2.1)
  - Dose (IU) = Body Weight (kg) × Desired factor VIII Rise (IU/dL or % of Normal) × 0.5 (IU/kg per IU/dL) (2.1)
  Routine prophylaxis:
- Administer 40-50 IU/kg body weight twice weekly in adults and adolescents (12 years and older). (2.1)
- Administer 55 IU/kg twice weekly in children (<12 years) with a maximum of 70 IU/kg. (2.1)
  - Adjust the dose and dosing intervals based on the patient's clinical response. (2.1)
- Inject intravenously over a period of less than or equal to 5 minutes (maximum infusion rate 10 mL per min). (2.3)

3 DOSAGE FORMS AND STRENGTHS

ADYNOVATE is available as a white to off-white lyophilized powder in single-dose vials containing nominally (approximately) 250, 500, 750, 1000, 1500, 2000, or 3000 international units. (3)

4 CONTRAINDICATIONS

Do not use in patients who have had prior anaphylactic reaction to ADYNOVATE, the parent molecule (ADVATE®), mouse or hamster protein, or excipients of ADYNOVATE. (4)

5 WARNINGS AND PRECAUTIONS

- Hypersensitivity reactions, including anaphylaxis, have been reported. Should symptoms occur, discontinue treatment with ADYNOVATE and administer appropriate treatment. (5.1)
- Development of factor VIII neutralizing antibodies (inhibitors) may occur. If expected plasma factor VIII activity levels are not attained, or if bleeding is not controlled with an appropriate dose, perform an assay that measures factor VIII inhibitor concentration. (5.2, 5.3)

6 ADVERSE REACTIONS

The most common adverse reactions reported in ≥1% of patients were cough, headache, diarrhea, vomiting, rash, nausea, urticaria, and dizziness. (6)

To report SUSPECTED ADVERSE REACTIONS, contact Takeda Pharmaceuticals U.S.A., Inc. at 1-877-TAKEDA-7 (1-877-825-3327) or FDA at 1-800-FDA-1088 or www.fda.gov/medwatch.

8 USE IN SPECIFIC POPULATIONS

Pediatric Use: Higher clearance, a shorter half-life and lower incremental recovery of factor VIII has been observed in children (<12 years). Dose adjustment or more frequent dosing based on per kg body weight may be needed in this population. (8.4)

FULL PRESCRIBING INFORMATION

1 INDICATIONS AND USAGE

ADYNOVATE® is indicated in adult and pediatric patients with hemophilia A (congenital factor VIII deficiency) for:

- On-demand treatment and control of bleeding episodes.
- Perioperative management.
- Routine prophylaxis to reduce the frequency of bleeding episodes.

Limitations of Use

ADYNOVATE is not indicated for the treatment of von Willebrand disease.

2 DOSAGE AND ADMINISTRATION

For intravenous use after reconstitution only.

2.1 Dose

- Each vial label of ADYNOVATE states the actual factor VIII potency in international units. This may be more or less than the nominal vial potency/content. One international unit corresponds to the activity of factor VIII contained in one milliliter of normal human plasma.
- Dosage and duration of treatment depend on the severity of factor VIII deficiency, the location and extent of the bleeding, and the patient's clinical condition. Careful monitoring of replacement therapy is necessary in cases of serious or life-threatening bleeding episodes.
- Potency assignment is determined using a one-stage clotting assay. Plasma factor VIII levels can be monitored clinically using a one-stage clotting assay.
- Calculate the dose of ADYNOVATE based on the empirical finding that one international unit of ADYNOVATE per kg body weight increases the plasma factor VIII level by 2 IU per dL of plasma. Use the following formula to estimate the expected in vivo peak increase in factor VIII level expressed as IU per dL (or % of normal) and the dose to achieve a desired in vivo peak increase in factor VIII level:

Estimated Increment of factor VIII (IU/dL or % of normal) = [Total Dose (IU)/body weight (kg)] × 2 (IU/dL per IU/kg)

Dose (IU) = Body Weight (kg) × Desired factor VIII Rise (IU/dL or % of Normal) × 0.5 (IU/kg per IU/dL)

- Patients vary in their pharmacokinetic (e.g., clearance, half-life, in vivo recovery) and clinical response. Base the dose and frequency of ADYNOVATE on the individual clinical response.

On-demand Treatment and Control of Bleeding Episodes

A guide for dosing of ADYNOVATE for the on-demand treatment and control of bleeding episodes is provided in Table 1. Maintain plasma factor VIII activity level at or above the described plasma levels (in IU per dL or % of normal).

Table 1: Dosing for On-demand Treatment and Control of Bleeding Episodes
Type of Bleeding | Target Factor VIII Level (IU/dL or % of normal) | Dose [Dose (IU/kg) = Desired factor VIII rise (IU/dL or % of normal) × 0.5 (IU/kg per IU/dL)] (IU/kg) | Frequency of Dosing (hours) | Duration of Therapy
Minor Early hemarthrosis, mild muscle bleeding, or mild oral bleeding episode. | 20-40 | 10-20 | 12-24 | Until the bleeding is resolved.
Moderate Muscle bleeding, moderate bleeding into the oral cavity, definite hemarthroses, and known trauma. | 30-60 | 15-30 | 12-24 | Until the bleeding is resolved.
Major Significant gastrointestinal bleeding, intracranial, intra-abdominal or intrathoracic bleeding, central nervous system bleeding, bleeding in the retropharyngeal or retroperitoneal spaces or iliopsoas sheath, fractures, head trauma. | 60-100 | 30-50 | 8-24 | Until the bleeding is resolved.

Perioperative Management

A guide for dosing ADYNOVATE during surgery (perioperative management) is provided in Table 2. Consideration should be given to maintain a factor VIII activity at or above the target range.

Table 2: Dosing for Perioperative Management
Type of Surgery | Factor VIII Level Required (% of normal or IU/dL) | Dose (IU/kg) | Frequency of Doses (hours) | Duration of Treatment
Minor Including tooth extraction. | 60-100 | 30-50 | Within one hour before surgery. Repeat after 24 hours if necessary. | Single dose or repeat as needed until bleeding is resolved.
Major Intracranial, intra-abdominal, or intrathoracic surgery, joint replacement surgery. | 80-120 (pre- and post-operative) | 40-60 | Within one hour before the operation to achieve 100% activity. Repeat every 8 to 24 hours (6 to 24 hours for patients <12 years of age) to maintain FVIII activity within the target range. | Until adequate wound healing.

Routine Prophylaxis

- Administer 40-50 IU/kg body weight twice weekly in adults and adolescents (12 years and older).
- Administer 55 IU per kg body weight two times per week in children (<12 years) with a maximum of 70 IU/kg.
- Adjust the dose and dosing intervals based on the patient’s clinical response.

2.2 Preparation and Reconstitution

Preparation

- Do not remove ADYNOVATE or diluent vials from the external housing.
- Examine the packaging containing ADYNOVATE to ensure no damage or peeling of the lid is evident. Do not use if the lid is not completely sealed on the blister.
- Use aseptic technique (clean and germ free) and a flat work surface during the reconstitution procedure.

Reconstitution

1. Allow the ADYNOVATE package to reach room temperature before use.
2. Open the package by peeling away the lid. Remove ADYNOVATE from the package and verify that the expiration date on the label has not passed and the potency unit number is same as expected. Inspect parenteral drug products for discoloration and particulate matter. The ADYNOVATE powder should be white to off-white in color and the diluent free from foreign particles. Do not use if the criteria are not met.
3. Place the ADYNOVATE on a flat surface with the diluent vial on top (Figure A). The diluent vial has a blue stripe. Do not remove the blue cap until instructed in a later step.
  Figure A
4. With one hand holding the ADYNOVATE housing, press down firmly on the diluent vial with the other hand until the system is fully collapsed and the diluent flows down into the ADYNOVATE vial (Figure B). Do not tilt the system until the transfer is complete.
  Figure B
5. Verify that diluent transfer is complete. Swirl gently until the powder is completely dissolved (Figure C). Do not shake. Do not refrigerate after reconstitution.
  Figure C

2.3 Administration

- Visually inspect the reconstituted ADYNOVATE solution for particulate matter and discoloration prior to administration, whenever solution and container permit. The final ADYNOVATE solution should be clear and colorless. Do not use if particulate matter or discoloration is observed.
- Administer ADYNOVATE as soon as possible, but no later than 3 hours after reconstitution.

Administration Steps:

1. Remove the blue cap from the housing. Connect the syringe to the system (Figure D). Do not inject air into the ADYNOVATE.
  Figure D
2. Turn the system upside down (ADYNOVATE vial now on top). Draw the ADYNOVATE solution into the syringe by pulling the plunger back slowly (Figure E).
  Figure E
3. Disconnect the syringe, attach a suitable needle, and inject intravenously as instructed. If a patient is to receive more than one ADYNOVATE -BAXJECT® III system or a combination of an ADYNOVATE -BAXJECT II and an ADYNOVATE -BAXJECT III system, the contents may be drawn into the same syringe.
4. Administer ADYNOVATE intravenously over a period of less than or equal to 5 minutes (maximum infusion rate 10 mL per min).

3 DOSAGE FORMS AND STRENGTHS

ADYNOVATE is available as a white to off-white lyophilized powder in single-dose vials containing nominally (approximately) 250, 500, 750, 1000, 1500, 2000, and 3000 International Units (IU, units). The 250-1500 IU strengths come with 2 mL Sterile Water for Injection (sWFI); the 2000 and 3000 IU strengths come with 5 mL of sWFI. The actual factor VIII potency/content is labeled on each ADYNOVATE vial.

The potency assignment employs a factor VIII concentrate standard that is referenced to a WHO (World Health Organization) international standard for factor VIII concentrates and is evaluated by appropriate methodology to ensure accuracy of the results.

4 CONTRAINDICATIONS

ADYNOVATE is contraindicated in patients who have had prior anaphylactic reaction to ADYNOVATE, to the parent molecule (ADVATE®), mouse or hamster protein, or excipients of ADYNOVATE (e.g. Tris, mannitol, trehalose, glutathione, and/or polysorbate 80).

5 WARNINGS AND PRECAUTIONS

5.1 Hypersensitivity Reactions

Hypersensitivity reactions including anaphylaxis, have been reported with ADYNOVATE. Hypersensitivity reactions that can progress to anaphylaxis may include angioedema, chest tightness, dyspnea, wheezing, urticaria, pruritus, and nausea and vomiting. Immediately discontinue administration and initiate appropriate treatment if hypersensitivity reactions occur.

5.2 Neutralizing Antibodies

Formation of neutralizing antibodies (inhibitors) to factor VIII can occur following administration of ADYNOVATE. Monitor patients regularly for the development of factor VIII inhibitors by appropriate clinical observations and laboratory tests. Perform an assay that measures factor VIII inhibitor concentration if the plasma factor VIII level fails to increase as expected, or if bleeding is not controlled with expected dose.

5.3 Monitoring Laboratory Tests

- Monitor plasma factor VIII activity by performing a validated one-stage clotting assay to confirm the adequate factor VIII levels have been achieved and maintained [see Dosage and Administration (2)].
- Monitor for the development of factor VIII inhibitors. Perform the Bethesda inhibitor assay to determine if factor VIII inhibitor is present. If expected factor VIII activity plasma levels are not attained, or if bleeding is not controlled with the expected dose of ADYNOVATE, use Bethesda Units (BU) to determine inhibitor levels.

6 ADVERSE REACTIONS

6.1 Clinical Trials Experience

Because clinical trials are conducted under widely varying conditions, adverse reaction rates observed in the clinical trials of a drug cannot be directly compared to rates in clinical trials of another drug and may not reflect the rates observed in practice.

The pooled safety database described in this section reflects exposure of ADYNOVATE in 478 previously treated patients (PTPs) and previously untreated patients (PUPs) with severe hemophilia A (factor VIII less than 1% of normal), who received at least one dose of ADYNOVATE in 7 clinical studies [see Immunogenicity (12.6) and Clinical Studies (14)]. The total number of infusions within the safety database is 92173. Table 3 lists the adverse reactions reported during clinical studies.

The most common adverse reactions (≥1% of patients) were cough, headache, diarrhea, vomiting, rash, nausea, urticaria, and dizziness.

Table 3: Adverse Reactions Reported for ADYNOVATE [Pooled safety analysis from 7 clinical studies.]
MedDRA System Organ Class | Adverse Reaction | Number of Patients n (%) (N=478)
Gastrointestinal Disorders | Diarrhea | 38 (8%)
Gastrointestinal Disorders | Vomiting | 26 (5%)
Gastrointestinal Disorders | Nausea | 8 (2%)
Respiratory, Thoracic and Mediastinal Disorders | Cough | 50 (10%)
Eye Disorders | Ocular Hyperaemia | 3 (0.6%)
Immune System Disorder | Hypersensitivitya | 2 (0.4%)
Nervous System Disorders | Headache | 41 (9%)
Nervous System Disorders | Dizziness | 7 (1%)
Skin and Subcutaneous Tissue Disorders | Rash | 16 (3%)
Skin and Subcutaneous Tissue Disorders | Urticaria | 9 (2%)
Skin and Subcutaneous Tissue Disorders | Rash Pruritic | 1 (0.2%)
Skin and Subcutaneous Tissue Disorders | Eyelid Rash | 1 (0.2%)
Vascular Disorders | Flushing | 1 (0.2%)
Investigations | Eosinophil Count Increased | 2 (0.4%)
Injury, Poisoning and Procedural Complications | Infusion Related Reaction | 2 (0.4%)
a The event of hypersensitivity was a mild transient non-serious rash, occurring in one 2-year old patient who had developed a previous rash while on ADYNOVATE.

Two cases of acute pancreatitis, with no precipitating cause identified in one case, were reported in adults during an extension study of the clinical trial which evaluated 216 patients. Administration of ADYNOVATE continued and both cases resolved.

6.2 Postmarketing Experience

Because postmarketing reporting of adverse reactions is voluntary and from a population of uncertain size, it is not always possible to reliably estimate the frequency of these reactions or establish a causal relationship to product exposure.

Immune System Disorders: Anaphylactic Reaction

8 USE IN SPECIFIC POPULATIONS

8.1 Pregnancy

Risk Summary

There are no data with ADYNOVATE use in pregnant women to inform a drug-associated risk. Animal reproduction studies have not been conducted with ADYNOVATE. It is unknown whether ADYNOVATE can cause fetal harm when administered to a pregnant woman or can affect reproduction capacity.

In the U.S. general population, the estimated background risk of major birth defect and miscarriage in clinically recognized pregnancies is 2-4% and 15-20%, respectively.

8.2 Lactation

Risk Summary

There is no information regarding the presence of ADYNOVATE in human milk, the effect on the breastfed infant, or the effects on milk production. The developmental and health benefits of breastfeeding should be considered along with the mother's clinical need for ADYNOVATE and any potential adverse effects on the breastfed infant from ADYNOVATE or from the underlying maternal condition.

8.4 Pediatric Use

The safety and efficacy of ADYNOVATE have been established in pediatric patients. The use of ADYNOVATE for routine prophylaxis, on-demand treatment of bleeding episodes, or perioperative management was supported by five clinical studies which included 115 previously treated pediatric patients 1 to 16 years of age (78 patients <12 years of age). The safety and efficacy of ADYNOVATE in routine prophylaxis and the treatment of bleeding episodes were comparable between pediatric patients and adults. [see Adverse Reactions (6), Clinical Pharmacology (12), and Clinical Studies (14)]

Pharmacokinetic studies in children (<12 years) have demonstrated higher clearance, a shorter half-life and lower incremental recovery of factor VIII compared to adults. Because clearance (based on per kg body weight) has been demonstrated to be higher in children (<12 years), dose adjustment or more frequent dosing based on per kg body weight may be needed in this population. [see Clinical Pharmacology (12.3)]

8.5 Geriatric Use

Clinical studies of ADYNOVATE did not include patients aged 65 years and over.

11 DESCRIPTION

ADYNOVATE, Antihemophilic Factor (Recombinant), PEGylated, is formulated as a sterile, non-pyrogenic, white to off-white lyophilized powder for reconstitution for intravenous injection. The product is supplied in single-dose vials containing nominal (approximate) potencies of 250, 500, 750, 1000, 1500, 2000, or 3000 international units (IU). Each vial of ADYNOVATE is labeled with the actual factor VIII activity in IU determined using one-stage clotting assay, using a reference material calibrated against a World Health Organization (WHO) International Standard for factor VIII concentrates. One IU, as defined by the WHO standard for blood coagulation factor VIII, human, is approximately equal to the level of factor VIII activity found in 1 mL of fresh pooled human plasma.

When reconstituted with 2 mL or 5 mL sterile water for injection, the final solution contains the following excipients and stabilizers in targeted amounts per mL of reconstituted product:

Stabilizer and Excipient | 2 mL Reconstitution (for 250, 500, 750, 1000, 1500 IU) Target (per mL) | 5 mL Reconstitution (for 2000, 3000 IU) Target (per mL)
Tris (hydroxymethyl) aminomethane | 3.05 mg | 1.22 mg
Calcium Chloride | 0.60 mg | 0.24 mg
Mannitol | 80 mg | 32 mg
Sodium Chloride | 13.15 mg | 5.26 mg
Trehalose Dihydrate | 20 mg | 8 mg
Glutathione | 0.2 mg | 0.08 mg
Histidine | 3.90 mg | 1.56 mg
Polysorbate 80 | 0.25 mg | 0.10 mg

ADYNOVATE contains no preservative. The specific activity of ADYNOVATE is 2700-8000 IU/mg protein.

ADYNOVATE is a recombinant full-length human coagulation factor VIII (2,332 amino acids with a molecular weight (MW) of 280 kDa) covalently conjugated with one or more molecules of polyethylene glycol (MW 20 kDa) [see Clinical Pharmacology (12.1)]. The therapeutic activity of ADYNOVATE is derived from its parent drug substance, ADVATE [Antihemophilic Factor (Recombinant)], which is produced by recombinant DNA technology from the CHO cell line. ADVATE is purified from the culture medium using a series of chromatography columns. The purification process includes an immunoaffinity chromatography step in which a monoclonal antibody directed against factor VIII is employed to selectively isolate the factor VIII from the medium. The production process includes a dedicated, viral inactivation solvent-detergent treatment step. The ADVATE molecule is then covalently conjugated with the polyethylene glycol, which mainly targets lysine residues.

The cell culture, pegylation, purification process and formulation used in the manufacture of ADYNOVATE do not use additives of human or animal origins.

12 CLINICAL PHARMACOLOGY

12.1 Mechanism of Action

ADYNOVATE, a PEGylated form of recombinant antihemophilic factor (ADVATE), [see Description (11)], temporarily replaces the missing coagulation factor VIII needed for effective hemostasis in congenital hemophilia A patients. ADYNOVATE exhibits an extended terminal half-life through pegylation of the parent molecule, ADVATE, which reduces binding to the physiological factor VIII clearance receptor (LRP1).

12.2 Pharmacodynamics

Hemophilia A is a disorder characterized by a deficiency of functional coagulation factor VIII, resulting in a prolonged, patient plasma clotting time as measured by the activated partial thromboplastin time (aPTT). Treatment with ADYNOVATE normalizes the aPTT over the effective dosing period. The administration of ADYNOVATE increases plasma levels of factor VIII and can temporarily correct the coagulation defect in hemophilia A patients.

12.3 Pharmacokinetics

The pharmacokinetics (PK) of ADYNOVATE were evaluated in a multicenter, prospective, open-label clinical trial (Study 1) [see Clinical Studies (14)] and compared with ADVATE in 26 patients prior to initiation of prophylactic treatment with ADYNOVATE and in 22 patients after 6 months of treatment with ADYNOVATE. A single dose of 45 IU/kg was utilized for both products. The PK parameters, as shown in Table 4, were based on plasma coagulation factor VIII activity measured by the one-stage clotting assay and are presented by age groups.

Incremental recovery was comparable between both products. The PK parameters determined after 6 months of prophylactic treatment with ADYNOVATE were consistent with the initial parameter estimates.

Pediatric Pharmacokinetics

Pharmacokinetic parameters calculated from 39 patients <18 years of age (intent-to-treat analysis) are available for 14 children (2 to <6 years), 17 older children (6 to <12 years) from Study 2 [see Clinical Studies (14)] and 8 adolescent patients (12 to <18 years of age) from Study 1 [see Clinical Studies (14)], as shown in Table 4. The mean clearance (based on body weight) of ADYNOVATE was higher and the mean half-life was lower in children <12 years of age than adults. A dose adjustment may be required in children <12 years of age.

Table 4: Pharmacokinetic Parameters (Arithmetic Mean ± SD)
PK Parameters | Pediatric Population PK with Sparse Sampling [Population PK model with 3 post-infusion samples based on randomized drawing schedule.] |  | Adult and Adolescent Individual PK with Full Sampling [Individual PK with 12 post-infusion samples.]
PK Parameters | <6 years N=14 | 6 to <12 years N=17 | 12 to <18 years N = 8 | ≥18 years N = 18
Terminal half-life [h] | 11.8 ± 2.43 | 12.4 ± 1.67 | 13.43 ± 4.05 | 14.69 ± 3.79
MRT [h] | 17.0 ± 3.50 | 17.8 ± 2.42 | 17.96 ± 5.49 | 20.27 ± 5.23
CL [mL/(kg∙h)] | 3.53 ± 1.29 | 3.11 ± 0.76 | 3.87 ± 3.31 (2.73 ± 0.93) [Estimated mean and SD calculated not including one patient whose clearance estimate was 11.8 mL/(kg.h). Median including all patients is 2.78 mL/(kg.h).] | 2.27 ± 0.84
Incremental Recovery [(IU/dL)/(IU/kg)] | 1.89 ± 0.49 | 1.95 ± 0.47 | 2.12 ± 0.60 | 2.66 ± 0.68
AUC0-Inf [IU∙h/dL] | 1947 ± 757 | 2012 ± 495 | 1642 ± 752 | 2264 ± 729
Vss [dL/kg] | 0.56 ± 0.12 | 0.54 ± 0.09 | 0.56 ± 0.18 | 0.43 ± 0.11
Cmax [IU/dL] | 115 ± 30 | 115 ± 33 | 95 ± 25 | 122 ± 29
Tmax [h] | - [Tmax could not be calculated for patients in the pediatric study as only one sample was drawn (15-30 minutes post-infusion) within the first 3 hours of the infusion.] | - | 0.26 ± 0.10 | 0.46 ± 0.29
Abbreviations: MRT: mean residence time; CL: clearance; CI: confidence interval; AUC: area under the curve; Vss: body weight adjusted volume of distribution at steady-state; Cmax: maximum observed activity; Tmax: time to reach the maximum concentration.

Incremental recovery was further evaluated in 99 patients (PUP) <6 years of age in a prospective, uncontrolled, open-label, multicenter trial. Incremental recovery remained relatively stable over time of treatment with mean (SD) incremental recovery values (1‑stage clotting method) of 1.670 (0.594) (IU/dL)/(IU/kg) (n=99), 1.617 (0.640) (IU/dL)/(IU/kg) (n=47), 1.805 (0.593) (IU/dL)/(IU/kg) (n=87), and 1.873 (0.440) (IU/dL)/(IU/kg) (n=89), at baseline, visit 3 (ED 15 ± 1), visit 6 (ED 40 ± 3), and trial completion/termination (ED 100 to 110), respectively.

12.6 Immunogenicity

The observed incidence of anti-drug antibodies (FVIII, PEG FVIII, PEG, CHO) is highly dependent on the sensitivity and specificity of the assay. Differences in assay methods preclude meaningful comparisons of the incidence of anti-drug antibodies to ADYNOVATE in the studies described below with the incidence of anti-drug antibodies in studies with other products.

Immunogenicity was evaluated during 7 clinical trials with ADYNOVATE in 365 previously treated patients and 120 previously untreated patients with severe hemophilia A.

Previously Treated Patients

In 6 clinical studies with previously treated patients, immunogenicity was evaluated by monitoring neutralizing (inhibitory) antibodies to FVIII and by measuring the development of binding IgG and IgM antibodies against factor VIII, PEGylated (PEG)-factor VIII, PEG and Chinese hamster ovary (CHO) protein using validated ELISA assays.

Two previously treated patients developed a transient low titer FVIII inhibitor at 0.6 BU/mL with ADYNOVATE, only one of which was confirmed with repeat testing. Both of these patients continued treatment without change in the dose of ADYNOVATE.

Out of 365 patients, thirty-six patients showed pre-existing antibodies to factor VIII (n=5), PEG-factor VIII (n=31) and/or PEG (n=6) prior to the first exposure to ADYNOVATE. Twenty-four patients who tested negative at screening developed transient antibodies against factor VIII (n=10), PEG-FVIII (n=16) and/or PEG (n=3) at one or two consecutive study visits. Binding antibodies that were detected prior to exposure to ADYNOVATE, that transiently developed during the trial or were still detectable at study completion or data cutoff could not be correlated to any impaired treatment efficacy or altered pharmacokinetic parameters. There was no causal relationship between observed adverse events and binding antibodies except in one patient where a causal relationship cannot be ruled out based on available data. No patient had pre-existing or treatment-emergent antibodies to CHO protein.

Previously Untreated Patients

In the clinical study with previously untreated patients, immunogenicity was evaluated by monitoring neutralizing (inhibitory) antibodies to FVIII and by measuring the development of binding IgG and IgM antibodies against factor VIII, PEGylated (PEG)-factor VIII, and PEG using validated ELISA assays.

Of the 120 dosed patients, 100 patients were evaluable for inhibitor development. Of these, 11 (11%) patients developed confirmed FVIII inhibitors after mean (SD) exposure days of 7.6 (4) to ADYNOVATE.

Of the 11 patients who developed inhibitors, 6 (55%) developed high titer inhibitors (>5 BU/mL) and 5 (45%) developed low titer inhibitors (≤5 BU/mL).

Of the 120 patients, 4 patients (3%) had preexisting IgG binding antibodies to FVIII, 13 patients (11%) had preexisting IgM binding antibodies to PEG, 11 patients (9%) had preexisting IgG binding antibodies to PEG FVIII, and 7 patients (6%) had preexisting IgM binding antibodies to PEGFVIII. Of the 120 patients, 59 patients developed transient binding non-neutralizing antibodies to FVIII, PEG FVIII, and PEG after exposure to ADYNOVATE. There was no identified clinically significant effect of anti-drug antibodies on pharmacokinetics, pharmacodynamics, safety, or effectiveness of ADYVONATE over the treatment duration.

13 NONCLINICAL TOXICOLOGY

13.1 Carcinogenesis, Mutagenesis, Impairment of Fertility

Long-term studies in animals to evaluate the carcinogenic potential of ADYNOVATE or studies to determine the effects of ADYNOVATE on genotoxicity or fertility have not been performed.

14 CLINICAL STUDIES

The efficacy of ADYNOVATE was evaluated in 4 clinical studies, as described below.

Study 1

The safety, efficacy, and PK of ADYNOVATE were evaluated in a multicenter, open-label, prospective, non-randomized, two-arm clinical trial (Study 261201, NCT01736475) that compared the efficacy of a twice weekly prophylactic treatment regimen to on-demand treatment and determined hemostatic efficacy in the treatment of bleeding episodes. A total of 137 male PTPs (12 to 65 years of age) with severe hemophilia A received at least one infusion with ADYNOVATE. Twenty-five of the 137 patients were adolescents (12 to less than 18 years of age).

Patients received either prophylactic treatment (n = 120) with ADYNOVATE at a dose of 40-50 IU per kg twice weekly or on-demand treatment (n = 17) with ADYNOVATE at a dose of 10-60 IU per kg for a 6-month period. The mean (SD) dose per prophylaxis infusion was 44.4 (3.9) IU per kg with a median dosing interval of 3.6 days. There were 91 out of 98 (93%) patients previously treated prophylactically prior to enrollment, who experienced a reduction in dosing frequency during routine prophylaxis in the trial, with a median reduction of 33.7% (approximately one more day between doses). One hundred eighteen of 120 (98%) prophylaxis patients remained on the starting recommended regimen without dose adjustment, and 2 patients increased their dose to 60 IU/kg during prophylaxis due to bleeding in target joints.

On-demand Treatment and Control of Bleeding Episodes

A total of 518 bleeding episodes were treated with ADYNOVATE in the per-protocol population, i.e. dosed according to the protocol specific dosing requirements. Of these, 361 bleeding episodes (n=17 patients) occurred in the on-demand arm and 157 (n=61 patients) occurred in the prophylaxis arm. The median dose per infusion to treat all bleeding episodes in the per-protocol population was 29 (Q1: 20.0; Q3: 39.2) IU per kg. The median dose per infusion to treat a minor, moderate, or severe/major bleeding episode in the per-protocol population was 25.5 (Q1: 16.9; Q3: 37.6) IU/kg, 30.9 (Q1: 23.0; Q3: 43.1) IU/kg, or 36.4 (Q1: 29.0; Q3: 44.5) IU/kg, respectively.

A total of 591 bleeding episodes were treated with ADYNOVATE in the treated population, which was identical to the safety analysis set of patients assigned to routine prophylaxis or on-demand treatment with ADYNOVATE and who received at least one dose of the product. Of these, 361 bleeding episodes (n=17 patients) occurred in the on-demand arm and 230 bleeding episodes (n=75 patients) occurred in the routine prophylaxis arm. Efficacy in control of bleeding episodes is summarized in Table 5.

Table 5: Summary of Efficacy in Control of Bleeding (Treated Population)
Bleeding Episode Etiology |  | All | Joint | Non-joint
Number of bleeds treated |  | 591 | 455 | 136
Number of infusions to treat bleeding episodes | 1 infusions: | 85.4% | 85.9% | 83.8%
Number of infusions to treat bleeding episodes | 2 infusions: | 10.8% | 10.8% | 11.0%
Number of infusions to treat bleeding episodes | Total (1 or 2 infusions): | 96.2% | 96.7% | 94.8%
Rate of success to treat bleeding episodes [Excellent defined as full relief of pain and objective signs of bleeding cessation; Good defined as definite pain relief and/or improvement in signs of bleeding; Fair defined as probable and/or slight relief of pain and slight improvement in signs of bleeding after a single infusion. Required more than 1 infusion for complete resolution; None defined as no improvement or condition worsened.] | Excellent or good | 95.3% | 95.8% | 93.4%

Routine Prophylaxis

A total of 120 patients (treated population) received a twice a week regimen in the prophylaxis arm, and an additional 17 patients were treated episodically in the on-demand arm. In the treated population, the median [mean] annualized bleed rate (ABR) in the on-demand treatment arm was 41.5 [40.8] compared to 1.9 [4.7] while on a twice a week prophylaxis regimen (Table 6). In the per-protocol population, the median [mean] annualized bleed rate (ABR) in the on-demand treatment arm was 41.5 [40.8] compared to 1.9 [3.7] while on a twice a week prophylaxis regimen. Using a negative binomial model to estimate the ABR, there was a significant reduction in the ABR (p <0.0001) for patients in the prophylaxis arm compared to the on-demand arm.

Table 6: Annualized Bleed Rate by Treatment for ≥ 12 Years of Age (Treated Population)
Bleeding Episode Etiology | On-Demand Treatment |  | Routine Prophylaxis Treatment
Bleeding Episode Etiology | Median | Mean (SD) | Median | Mean (SD)
Overall | 41.5 | 40.8 (16.3) | 1.9 | 4.7 (8.6)
Joint | 38.1 | 34.7 (15.1) | 0.0 | 2.9 (8.0)
Non-Joint | 3.7 | 6.1 (6.7) | 0.0 | 1.8 (3.0)
Spontaneous | 21.6 | 26.0 (19.6) | 0.0 | 2.9 (7.1)
Traumatic | 9.3 | 14.9 (15.3) | 0.0 | 1.8 (3.1)

In the treated population, the median [mean] ABR for the 23 adolescent patients age 12 to <18 years of age on routine prophylaxis was 2.1 [5.2] compared to a median [mean] ABR of 1.9 [4.6] for the 97 patients 18 years and older. Reduction in ABR between the treatment arms was observed regardless of baseline subgroups examined, including age, presence or absence of target joints, and pre-trial treatment regimen. The majority of the bleeding episodes during prophylaxis (95%) were of minor/moderate severity. Forty-five out of 120 patients (38%) experienced no bleeding episodes and 68 out of 120 patients (57%) experienced no joint bleeding episodes in the prophylaxis arm. Of those patients who were compliant to regimen (per-protocol population), 40 out of 101 patients (40%) experienced no bleeding episodes. All patients in the on-demand arm experienced a bleeding episode, including a joint bleeding episode.

Study 2

Routine Prophylaxis Clinical Trial in Pediatric Patients (<12 years of age)

The safety and efficacy of ADYNOVATE was evaluated in a total of 73 pediatric PTPs with severe hemophilia A, of which 66 patients were dosed (32 patients aged <6 years and 34 patients aged 6 to <12 years) in a separate pediatric clinical trial (Study 261202, NCT02210091). The prophylactic regimen was 40 to 60 IU/kg of ADYNOVATE twice a week, with a mean (SD) dose of 51.1 IU/kg (5.5). The median [mean] overall ABR was 2.0 [3.61] for the 66 patients in the treated population and the median [mean] ABRs for spontaneous and joint bleeding episodes were both 0 [1.18 and 1.12, respectively]. Of the 66 patients treated prophylactically, 25 (38%) experienced no bleeding episodes, 44 (67%) experienced no spontaneous bleeding episodes, and 48 (73%) experienced no joint bleeding episodes.

Of the 70 bleeding episodes observed during the pediatric trial, 82.9% were controlled with 1 infusion and 91.4% were controlled with 1 or 2 infusions. Control of bleeding was rated excellent or good in 63 out of 70 (90%) bleeding episodes. The definitions of excellent or good in the pediatric clinical trial were unchanged as compared to the previously conducted prophylaxis clinical trial in adolescent and adult patients.

Study 3

An extension study (Study 261302, NCT01945593) in adult and pediatric patients evaluated the safety and efficacy of prophylactic treatment regimen in 216 previously treated patients with severe hemophilia A. Majority had completed the adult and adolescent study or the pediatric study. Similar efficacy was noted in this extension study.

Study 4

Perioperative Management Clinical Trial

The safety and efficacy of ADYNOVATE in PTPs (aged 12 to 65 years) with severe hemophilia A, who were undergoing elective surgical or other invasive procedures, was evaluated in a multicenter, open-label clinical trial (Study 261204, NCT01913405). In this clinical trial 21 major surgical procedures comprising of 14 orthopedic, and 7 non-orthopedic procedures, and 5 additional minor surgeries were performed in 21 patients. The preoperative loading dose ranged from 36 IU/kg to 99 IU/kg (median: 60 IU/kg) and the total post-operative dose ranged from 23 IU/kg to 769 IU/kg (median: 183 IU/kg). The median total dose (including all administrations from pre-surgical PK and loading doses to post-hospital follow up) was 629 IU/kg (range: 464 – 1,457 IU/kg) for major orthopedic surgeries, 489 IU/kg (range: 296 – 738 IU/kg) for major non-orthopedic surgeries.

Overall hemostatic efficacy was rated as excellent (blood loss less than or equal to that expected for the same type of procedure performed in a non-hemophilic patient, for all 24 (21 major, 3 minor) procedures with available assessments.

16 HOW SUPPLIED/STORAGE AND HANDLING

How Supplied

ADYNOVATE in a BAXJECT III system is packaged with 2 mL or 5 mL of Sterile Water for Injection, one Terumo Microbore Infusion set (2 mL only), one full prescribing physician insert and one patient insert. Components not made with natural rubber latex.

ADYNOVATE is available in single-dose vials that contain the following nominal product strengths:

Nominal Strength | Potency Color Code | Carton NDC (Includes 2 mL sWFI Diluent) | Carton NDC (Includes 5 mL sWFI Diluent)
250 IU | Light Blue | 0944-4622-01
500 IU | Pink | 0944-4623-01
750 IU | Red | 0944-4626-01
1000 IU | Light Green | 0944-4624-01
1500 IU | Purple | 0944-4627-01
2000 IU | Orange |  | 0944-4625-01
3000 IU | Silver |  | 0944-4628-01

Actual factor VIII activity in IU is stated on the label of each ADYNOVATE carton and housing.

Storage and Handling

- Store ADYNOVATE in powder form at 2°C to 8°C (36°F to 46°F).
- Do not freeze.
- ADYNOVATE may be stored at room temperature not to exceed 30°C (86°F) for a period of up to 3 months not to exceed the expiration date. If stored at room temperature, write the date on the carton when ADYNOVATE is removed from refrigeration.
- After storage at room temperature, do not return the product to the refrigerator.
- Do not use beyond expiration date printed on the carton or housing.
- Store ADYNOVATE in the original box and protect from extreme exposure to light.

17 PATIENT COUNSELING INFORMATION

Advise the patients to:

- Read the FDA-approved patient labeling (Patient Information and Instructions for Use).
- Call their healthcare provider or go to the emergency department right away if a hypersensitivity reaction occurs. Early signs of hypersensitivity reactions may include rash, hives, itching, facial swelling, tightness of the chest, and wheezing. Advise patients to discontinue use of the product if these symptoms occur and seek immediate emergency treatment.
- Contact their healthcare provider or treatment facility for further treatment and/or assessment if they experience a lack of a clinical response to factor VIII therapy because this may be a sign of inhibitor development.
- Consult with their physicians or healthcare provider prior to travel. While traveling, advise patients to bring an adequate supply of ADYNOVATE based on their current regimen of treatment.

To enroll in the confidential, industry-wide Patient Notification System, call 1-888-873-2838.

Takeda Pharmaceuticals U.S.A., Inc.
Cambridge, MA 02142
U.S. License No. 1898

ADYNOVATE, ADVATE and BAXJECT are registered trademarks of Baxalta Incorporated.

Takeda and are registered trademarks of Takeda Pharmaceutical Company Limited.

©2025 Takeda Pharmaceutical Company Limited. All rights reserved.

Patented: see www.takeda.com/en-us/patents

Patient Information
ADYNOVATE® (ah-DYE-noh-vayt)
[Antihemophilic Factor (Recombinant), PEGylated]

This leaflet summarizes important information about ADYNOVATE. Please read it carefully before using this medicine. This information does not take the place of talking with your healthcare provider, and it does not include all of the important information about ADYNOVATE. If you have any questions after reading this, ask your healthcare provider.

What is the most important information I need to know about ADYNOVATE?

Do not attempt to do an infusion to yourself unless you have been taught how by your healthcare provider or hemophilia center.

You must carefully follow your healthcare provider's instructions regarding the dose and schedule for infusing ADYNOVATE so that your treatment will work best for you.

What is ADYNOVATE?

ADYNOVATE is an injectable medicine that is used to help treat and control bleeding in adults and children with hemophilia A (congenital Factor VIII deficiency). Your healthcare provider may give you ADYNOVATE when you have surgery.

ADYNOVATE can reduce the number of bleeding episodes when used regularly (prophylaxis).

ADYNOVATE is not used to treat von Willebrand disease.

Who should not use ADYNOVATE?

You should not use ADYNOVATE if you:

- Are allergic to mice or hamster protein
- Are allergic to any ingredients in ADYNOVATE or ADVATE®

Tell your healthcare provider if you are pregnant or breastfeeding because ADYNOVATE may not be right for you.

How should I use ADYNOVATE?

ADYNOVATE is given directly into the bloodstream.

You may infuse ADYNOVATE at a hemophilia treatment center, at your healthcare provider's office or in your home. You should be trained on how to do infusions by your healthcare provider or hemophilia treatment center. Many people with hemophilia A learn to infuse their ADYNOVATE by themselves or with the help of a family member.

Your healthcare provider will tell you how much ADYNOVATE to use based on your individual weight, level of physical activity, the severity of your hemophilia A, and where you are bleeding.

Reconstituted product (after mixing dry product with wet diluent) must be used within 3 hours and cannot be stored or refrigerated. Discard any ADYNOVATE left in the vial at the end of your infusion as directed by your healthcare professional.

You may have to have blood tests done after getting ADYNOVATE to be sure that your blood level of factor VIII is high enough to clot your blood.

Call your healthcare provider right away if your bleeding does not stop after taking ADYNOVATE.

What should I tell my healthcare provider before I use ADYNOVATE?

You should tell your healthcare provider if you:

- Have or have had any medical problems.
- Take any medicines, including prescription and non-prescription medicines, such as over-the-counter medicines, supplements or herbal remedies.
- Have any allergies, including allergies to mice or hamsters.
- Are breastfeeding. It is not known if ADYNOVATE passes into your milk and if it can harm your baby.
- Are pregnant or planning to become pregnant. It is not known if ADYNOVATE may harm your unborn baby.
- Have been told that you have inhibitors to factor VIII (because ADYNOVATE may not work for you).

What are the possible side effects of ADYNOVATE?

You can have an allergic reaction to ADYNOVATE.

Call your healthcare provider right away and stop treatment if you get a rash or hives, itching, tightness of the throat, chest pain or tightness, difficulty breathing, lightheadedness, dizziness, nausea or fainting.

The common side effects of ADYNOVATE are cough, headache, diarrhea, vomiting, rash, nausea, hives, and dizziness. Tell your healthcare provider about any side effects that bother you or do not go away.

These are not all the possible side effects with ADYNOVATE. You can ask your healthcare provider for information that is written for healthcare professionals.

What are the ADYNOVATE dosage strengths?

ADYNOVATE with 2 mL or 5 mL Sterile Water for Injection in a BAXJECT® III system comes in seven different dosage strengths: 250 International Units (IU), 500 IU, 750 IU, 1000 IU, 1500 IU, 2000 IU, and 3000 IU. The actual strength will be imprinted on the label and on the box. The seven different strengths are color coded, as follows:

Dosage strength of approximately 250 International Units per vial (with 2 mL sWFI)

Dosage strength of approximately 500 International Units per vial (with 2 mL sWFI)

Dosage strength of approximately 750 International Units per vial (with 2 mL sWFI)

Dosage strength of approximately 1000 International Units per vial (with 2 mL sWFI)

Dosage strength of approximately 1500 International Units per vial (with 2 mL sWFI)

Dosage strength of approximately 2000 International Units per vial (with 5 mL sWFI)

Dosage strength of approximately 3000 International Units per vial (with 5 mL sWFI)

Always check the actual dosage strength printed on the label to make sure you are using the strength prescribed by your healthcare provider. Always check the expiration date printed on the box. Do not use the product after the expiration date printed on the box.

How do I store ADYNOVATE?

- Do not freeze.
- Store at refrigerated temperature 2°C to 8°C (36°F to 46°F).
- May store at room temperature not to exceed 30°C (86°F) for up to 3 months.
  - Write the date on the carton when ADYNOVATE is removed from refrigeration.
  - After storage at room temperature, do not return product back to the refrigerator.
- Do not use beyond the expiration date printed on the carton or vial.
- Store ADYNOVATE in the original box and protect from extreme exposure to light.

What else should I know about ADYNOVATE and Hemophilia A?

Your body may form inhibitors to Factor VIII. An inhibitor is part of the body's normal defense system. If you form inhibitors, it may stop ADYNOVATE from working properly. Consult with your healthcare provider to make sure you are carefully monitored with blood tests for the development of inhibitors to Factor VIII.

Medicines are sometimes prescribed for purposes other than those listed here. Do not use ADYNOVATE for a condition for which it is not prescribed. Do not share ADYNOVATE with other people, even if they have the same symptoms that you have.

Takeda Pharmaceuticals U.S.A., Inc.
Cambridge, MA 02142
U.S. License No. 1898

ADYNOVATE, ADVATE and BAXJECT are registered trademarks of Baxalta Incorporated.

Takeda and are registered trademarks of Takeda Pharmaceutical Company Limited.

©2025 Takeda Pharmaceutical Company Limited. All rights reserved.

Patented: see www.takeda.com/en-us/patents

This Patient Information has been approved by the U.S. Food and Drug Administration.

Revised: 10/2025

Instructions For Use
ADYNOVATE®
[Antihemophilic Factor (Recombinant), PEGylated]
(For intravenous use only)

Do not attempt to do an infusion to yourself unless you have been taught how by your healthcare provider or hemophilia center.

Step-by-step instructions for reconstituting ADYNOVATE are found at the end of this leaflet.

Always follow the specific instructions given by your healthcare provider. The steps listed below are general guidelines for using ADYNOVATE. If you are unsure of the procedures, please call your healthcare provider before using.

Call your healthcare provider right away if bleeding is not controlled after using ADYNOVATE.

Your healthcare provider will prescribe the dose that you should take.

Reconstituted product (after mixing dry product with wet diluent) must be used within 3 hours and cannot be stored or refrigerated.

Your healthcare provider may need to take blood tests from time to time.

Talk to your healthcare provider before traveling. Plan to bring enough ADYNOVATE for your treatment during this time.

Dispose of all materials, including any leftover reconstituted ADYNOVATE product, in an appropriate container.

1. Prepare a clean flat surface and gather all the materials you will need for the infusion.
  - Check the expiration date, and let the ADYNOVATE warm up to room temperature.
  - Wash your hands and put on clean exam gloves. If infusing yourself at home, the use of gloves is optional.
2. Open the ADYNOVATE package by peeling away the lid. Remove the ADYNOVATE from the package and visually inspect the contents of the product and diluent vial. The ADYNOVATE powder should be white to off-white in color and the diluent should not contain particles. Do not use if discoloration or particles are seen.
3. Place on a flat surface with the diluent vial on top. The diluent vial has a blue stripe.
4. With one hand holding the ADYNOVATE housing, press down firmly on the diluent vial with the other hand until the system is fully collapsed and the diluent flows down into the ADYNOVATE vial. Both vials will move into the housing when pressed. If you don't see the diluent transfer to the product vial, press the vials again to assure they are completely inserted. Do not remove the blue cap until instructed in a later step.
5. Swirl the ADYNOVATE gently and continuously until the ADYNOVATE is completely dissolved. Do not shake. Do not refrigerate after reconstitution. Inspect the ADYNOVATE solution for particulate matter and discoloration prior to administration. The solution should be clear and colorless in appearance. If not, do not use the solution and notify your healthcare provider immediately.
6. Take off the blue cap from the housing and connect the syringe. Be careful to not inject air into the ADYNOVATE.
7. Turn over the ADYNOVATE so that the vial containing the ADYNOVATE solution is on top. Draw the ADYNOVATE solution into the syringe by pulling back the plunger slowly. If the solution does not draw into the syringe, be sure that both vials are pressed firmly together. The contents of more than one vial may be drawn into a single, appropriately sized syringe if you are using more than one vial of ADYNOVATE.
8. Disconnect the syringe from the system. Attach the infusion needle to the syringe using a winged (butterfly) infusion set, if available. Point the needle up and remove any air bubbles by gently tapping the syringe with your finger and slowly and carefully pushing air out of the syringe and needle.
9. Apply a tourniquet and get the injection site ready by wiping the skin well with an alcohol swab (or other suitable solution suggested by your healthcare provider or hemophilia center).
10. Insert the needle into the vein and remove the tourniquet. Slowly infuse the ADYNOVATE. Do not infuse any faster than 10 mL per minute.
11. Take the needle out of the vein and use sterile gauze to put pressure on the infusion site for several minutes.
12. Remove the peel-off label from blister lid and place it in your logbook. Clean any spilled blood with a freshly prepared mixture of 1 part bleach and 9 parts water, soap and water, or any household disinfecting solution.
13. Do not recap the needle. Place needle, syringe and ADYNOVATE system in a hard-walled Sharps container for proper disposal. Do not dispose of these supplies in ordinary household trash.

Important: Contact your healthcare provider or local hemophilia treatment center if you experience any problems.

Takeda Pharmaceuticals U.S.A., Inc.
Cambridge, MA 02142
U.S. License No. 1898

ADYNOVATE is a registered trademark of Baxalta Incorporated.

Takeda and are registered trademarks of Takeda Pharmaceutical Company Limited.

©2025 Takeda Pharmaceutical Company Limited. All rights reserved.

Patented: see www.takeda.com/en-us/patents

Revised: 10/2025

PRINCIPAL DISPLAY PANEL - Kit Carton - 250 IU

ADYNOVATE®
[Antihemophilic Factor
(Recombinant), PEGylated]

NDC 0944-4622-01

Single-dose only

For Intravenous Administration After Reconstitution Only

Lyophilized powder for reconstitution

ADYNOVATE and diluent preassembled in BAXJECT III system

Rx Only

Actual potency

Takeda

PRINCIPAL DISPLAY PANEL - Barrel Label - 250 IU

ADYNOVATE®
[Antihemophilic Factor
(Recombinant), PEGylated]

For Intravenous Administration Only

ADYNOVATE and diluent preassembled
in BAXJECT® III system

Directions for use: see package insert

Rx Only

IU:

LOT:

EXP:

Takeda

6521221

PRINCIPAL DISPLAY PANEL - Blister Label - 250 IU

ADYNOVATE®
[Antihemophilic Factor
(Recombinant), PEGylated]

NDC 0944-4622-02

Single-dose only

6521479

For Intravenous Administration Only

ADYNOVATE and diluent preassembled in BAXJECT® III system

Do not open until time of use

Do not use if packaging is opened or damaged

Discard unused portion.

Rx Only

Takeda

PRINCIPAL DISPLAY PANEL - Kit Carton - 500 IU

ADYNOVATE®
[Antihemophilic Factor
(Recombinant), PEGylated]

NDC 0944-4623-01

Single-dose only

For Intravenous Administration After Reconstitution Only

Lyophilized powder for reconstitution

ADYNOVATE and diluent preassembled in BAXJECT III system

Rx Only

Actual potency

Takeda

PRINCIPAL DISPLAY PANEL - Barrel Label - 500 IU

ADYNOVATE®
[Antihemophilic Factor
(Recombinant), PEGylated]

For Intravenous Administration Only

ADYNOVATE and diluent preassembled
in BAXJECT® III system

Directions for use: see package insert

Rx Only

IU:

LOT:

EXP:

Takeda

6521223

PRINCIPAL DISPLAY PANEL - Blister Label - 500 IU

ADYNOVATE®
[Antihemophilic Factor
(Recombinant), PEGylated]

NDC 0944-4623-02

Single-dose only

6521484

For Intravenous Administration Only

ADYNOVATE and diluent preassembled in BAXJECT® III system

Do not open until time of use

Do not use if packaging is opened or damaged

Discard unused portion.

Rx Only

Takeda

PRINCIPAL DISPLAY PANEL - Kit Carton - 750 IU

ADYNOVATE®
[Antihemophilic Factor
(Recombinant), PEGylated]

NDC 0944-4626-01

Single-dose only

For Intravenous Administration After Reconstitution Only

Lyophilized powder for reconstitution

ADYNOVATE and diluent preassembled in BAXJECT III system

Rx Only

Actual potency

Takeda

PRINCIPAL DISPLAY PANEL - Barrel Label - 750 IU

ADYNOVATE®
[Antihemophilic Factor
(Recombinant), PEGylated]

For Intravenous Administration Only

ADYNOVATE and diluent preassembled
in BAXJECT® III system

Directions for use: see package insert

Rx Only

IU:

LOT:

EXP:

Takeda

6521228

PRINCIPAL DISPLAY PANEL - Blister Label - 750 IU

ADYNOVATE®
[Antihemophilic Factor
(Recombinant), PEGylated]

NDC 0944-4626-02

Single-dose only

6521490

For Intravenous Administration Only

ADYNOVATE and diluent preassembled in BAXJECT® III system

Do not open until time of use

Do not use if packaging is opened or damaged

Discard unused portion.

Rx Only

Takeda

PRINCIPAL DISPLAY PANEL - Kit Carton - 1000 IU

ADYNOVATE®
[Antihemophilic Factor
(Recombinant), PEGylated]

NDC 0944-4624-01

Single-dose only

For Intravenous Administration After Reconstitution Only

Lyophilized powder for reconstitution

ADYNOVATE and diluent preassembled in BAXJECT III system

Rx Only

Actual potency

Takeda

PRINCIPAL DISPLAY PANEL - Barrel Label - 1000 IU

ADYNOVATE®
[Antihemophilic Factor
(Recombinant), PEGylated]

For Intravenous Administration Only

ADYNOVATE and diluent preassembled
in BAXJECT® III system

Directions for use: see package insert

Rx Only

IU:

LOT:

EXP:

Takeda

6521224

PRINCIPAL DISPLAY PANEL - Blister Label - 1000 IU

ADYNOVATE®
[Antihemophilic Factor
(Recombinant), PEGylated]

NDC 0944-4624-02

Single-dose only

6521493

For Intravenous Administration Only

ADYNOVATE and diluent preassembled in BAXJECT® III system

Do not open until time of use

Do not use if packaging is opened or damaged

Discard unused portion.

Rx Only

Takeda

PRINCIPAL DISPLAY PANEL - Kit Carton - 1500 IU

ADYNOVATE®
[Antihemophilic Factor
(Recombinant), PEGylated]

NDC 0944-4627-01

Single-dose only

For Intravenous Administration After Reconstitution Only

Lyophilized powder for reconstitution

ADYNOVATE and diluent preassembled in BAXJECT III system

Rx Only

Actual potency

Takeda

PRINCIPAL DISPLAY PANEL - Barrel Label - 1500 IU

ADYNOVATE®
[Antihemophilic Factor
(Recombinant), PEGylated]

For Intravenous Administration Only

ADYNOVATE and diluent preassembled
in BAXJECT® III system

Directions for use: see package insert

Rx Only

IU:

LOT:

EXP:

Takeda

6521225

PRINCIPAL DISPLAY PANEL - Blister Label - 1500 IU

ADYNOVATE®
[Antihemophilic Factor
(Recombinant), PEGylated]

NDC 0944-4627-02

Single-dose only

6521495

For Intravenous Administration Only

ADYNOVATE and diluent preassembled in BAXJECT® III system

Do not open until time of use

Do not use if packaging is opened or damaged

Discard unused portion.

Rx Only

Takeda

PRINCIPAL DISPLAY PANEL - Kit Carton - 2000 IU

ADYNOVATE®
[Antihemophilic Factor
(Recombinant), PEGylated]

NDC 0944-4625-01

Single-dose only

For Intravenous Administration After Reconstitution Only

Lyophilized powder for reconstitution

ADYNOVATE and diluent
preassembled in
BAXJECT III system

Rx Only

Actual potency

Takeda

PRINCIPAL DISPLAY PANEL - Barrel Label - 2000 IU

ADYNOVATE®
[Antihemophilic Factor
(Recombinant), PEGylated]

For Intravenous Administration Only

ADYNOVATE and diluent preassembled
in BAXJECT® III system

Directions for use: see package insert

Rx Only

IU:

LOT:

EXP:

Takeda

6521226

PRINCIPAL DISPLAY PANEL - Blister Label - 2000 IU

ADYNOVATE®
[Antihemophilic Factor
(Recombinant), PEGylated]

NDC 0944-4625-02

Single-dose only

6521498

For Intravenous Administration Only

ADYNOVATE and diluent preassembled in BAXJECT® III system

Do not open until time of use

Do not use if packaging is opened or damaged

Discard unused portion.

Rx Only

Takeda

PRINCIPAL DISPLAY PANEL - Kit Carton - 3000 IU

ADYNOVATE®
[Antihemophilic Factor
(Recombinant), PEGylated]

NDC 0944-4628-01

Single-dose only

For Intravenous Administration After Reconstitution Only

Lyophilized powder for reconstitution

ADYNOVATE and diluent
preassembled in
BAXJECT III system

Rx Only

Actual potency

Takeda

PRINCIPAL DISPLAY PANEL - Barrel Label - 3000 IU

ADYNOVATE®
[Antihemophilic Factor
(Recombinant), PEGylated]

For Intravenous Administration Only

ADYNOVATE and diluent preassembled
in BAXJECT® III system

Directions for use: see package insert

Rx Only

IU:

LOT:

EXP:

Takeda

6521227

PRINCIPAL DISPLAY PANEL - Blister Label - 3000 IU

ADYNOVATE®
[Antihemophilic Factor
(Recombinant), PEGylated]

NDC 0944-4628-02

Single-dose only

6521500

For Intravenous Administration Only

ADYNOVATE and diluent preassembled in BAXJECT® III system

Do not open until time of use

Do not use if packaging is opened or damaged

Discard unused portion.

Rx Only

Takeda

PRINCIPAL DISPLAY PANEL - Antihemophilic Factor Vial Label

Antihemophilic Factor (Recombinant), PEGylated

6521222

Takeda

Lot No.:

PRINCIPAL DISPLAY PANEL - Sterile Water for Injection Vial Label

Sterile Water for Injection

Lot No.:

Siegfried Hameln GmbH

0742211